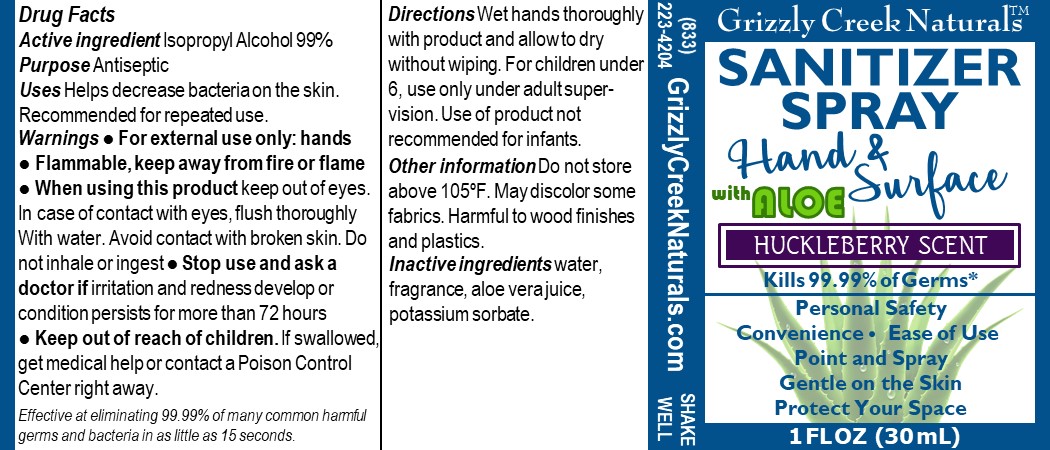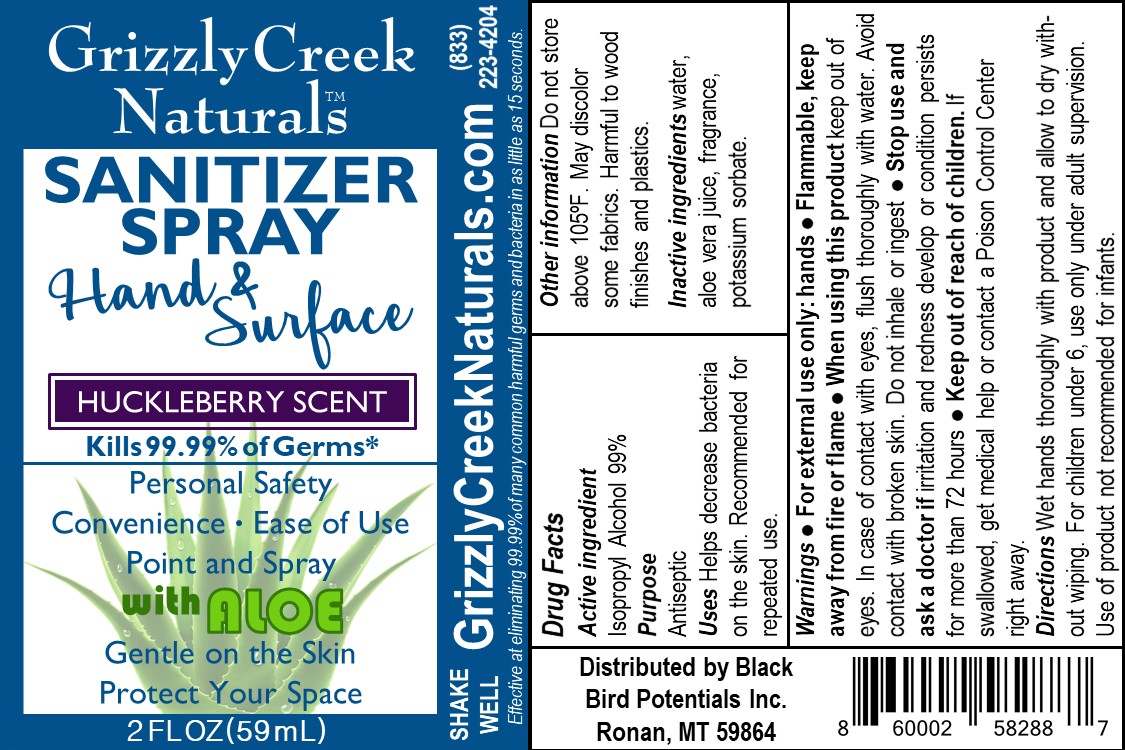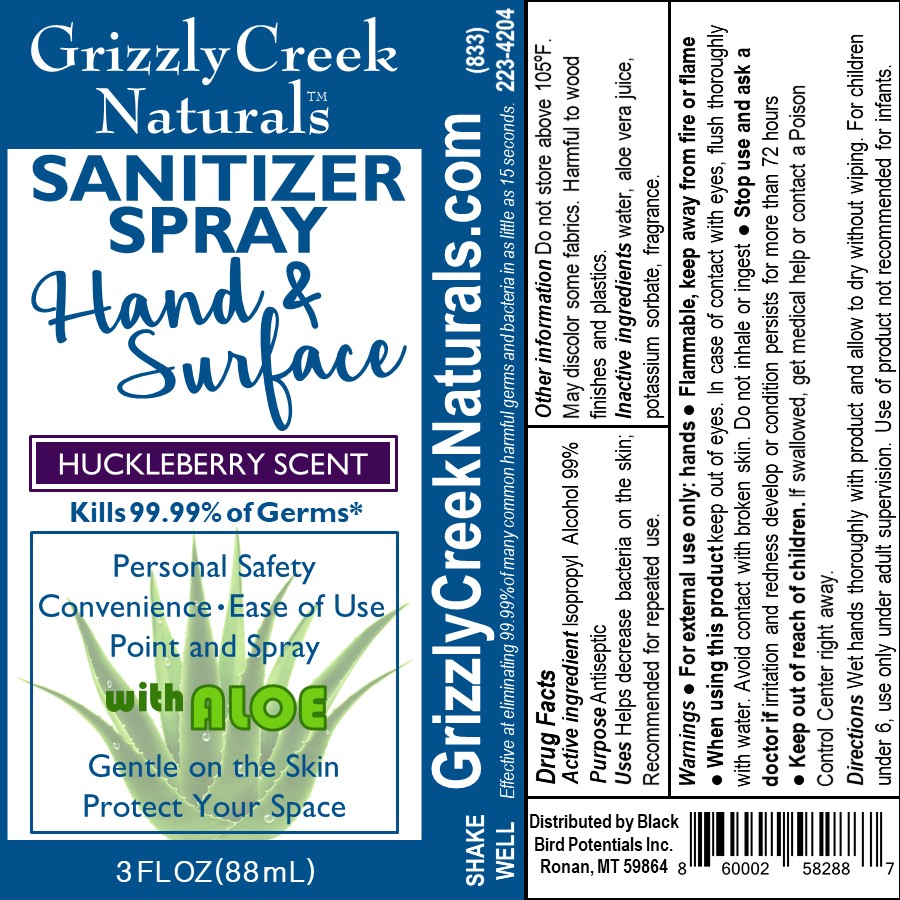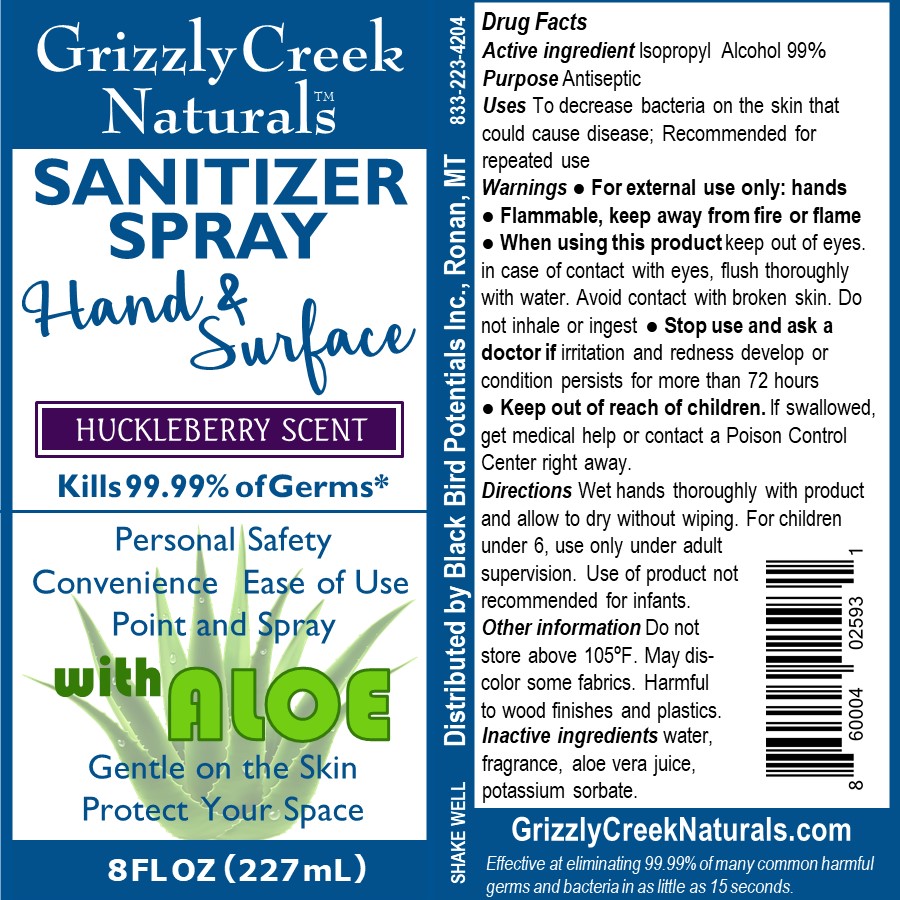 DRUG LABEL: Grizzly Creek Naturals Sanitizer Huckleberry
NDC: 73816-201 | Form: SPRAY
Manufacturer: BLACK BIRD POTENTIALS INC.
Category: otc | Type: HUMAN OTC DRUG LABEL
Date: 20200501

ACTIVE INGREDIENTS: ISOPROPYL ALCOHOL 0.7 mL/1 mL
INACTIVE INGREDIENTS: POTASSIUM SORBATE; WATER; ALOE ARBORESCENS LEAF

Drug Facts

Active ingredient Isopropyl Alcohol 99%

Purpose Antiseptic

PURPOSE

Uses Helps decrease bacteria on the skin. Recommended for repeated use.

WARNINGS

Warnings ● For external use only: hands ● Flammable, keep away from fire or flame

When using this product keep out of eyes. In case of contact with eyes, flush thoroughly with water. Avoid contact with broken skin. Do not inhale or ingest

Stop use and ask a doctor if irritation and redness develop or condition persists for more than 72 hours

Keep out of reach of children. If swallowed, get medical help or contact a Poison Control Center right away.

Other information Do not store above 105ºF. May discolor some fabrics. Harmful to wood finishes and plastics.

INACTIVE INGREDIENT

Inactive ingredients water, aloe vera juice, fragrance, potassium sorbate.

DOSAGE AND ADMINISTRATION

Directions Wet hands thoroughly with product and allow to dry without wiping. For children under 6, use only under adult supervision. Use of product not recommended for infants.

INDICATIONS AND USAGE

Uses Helps decrease bacteria on the skin. Recommended for repeated use.

PACKAGE LABEL

30 mL NDC: 73816-201-01

PACKAGE LABEL

59 mL NDC: 73816-201-02

PACKAGE LABEL

88 mL NDC: 73816-201-03

PACKAGE LABEL

227 mL NDC: 73816-201-04